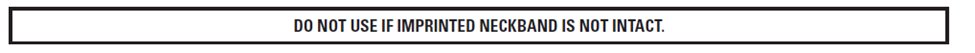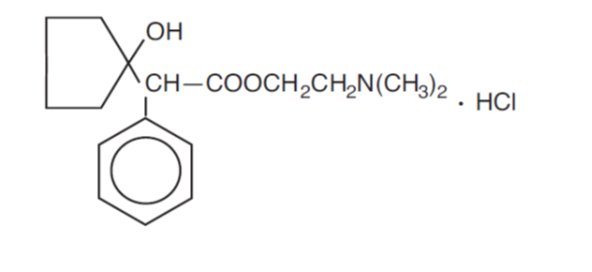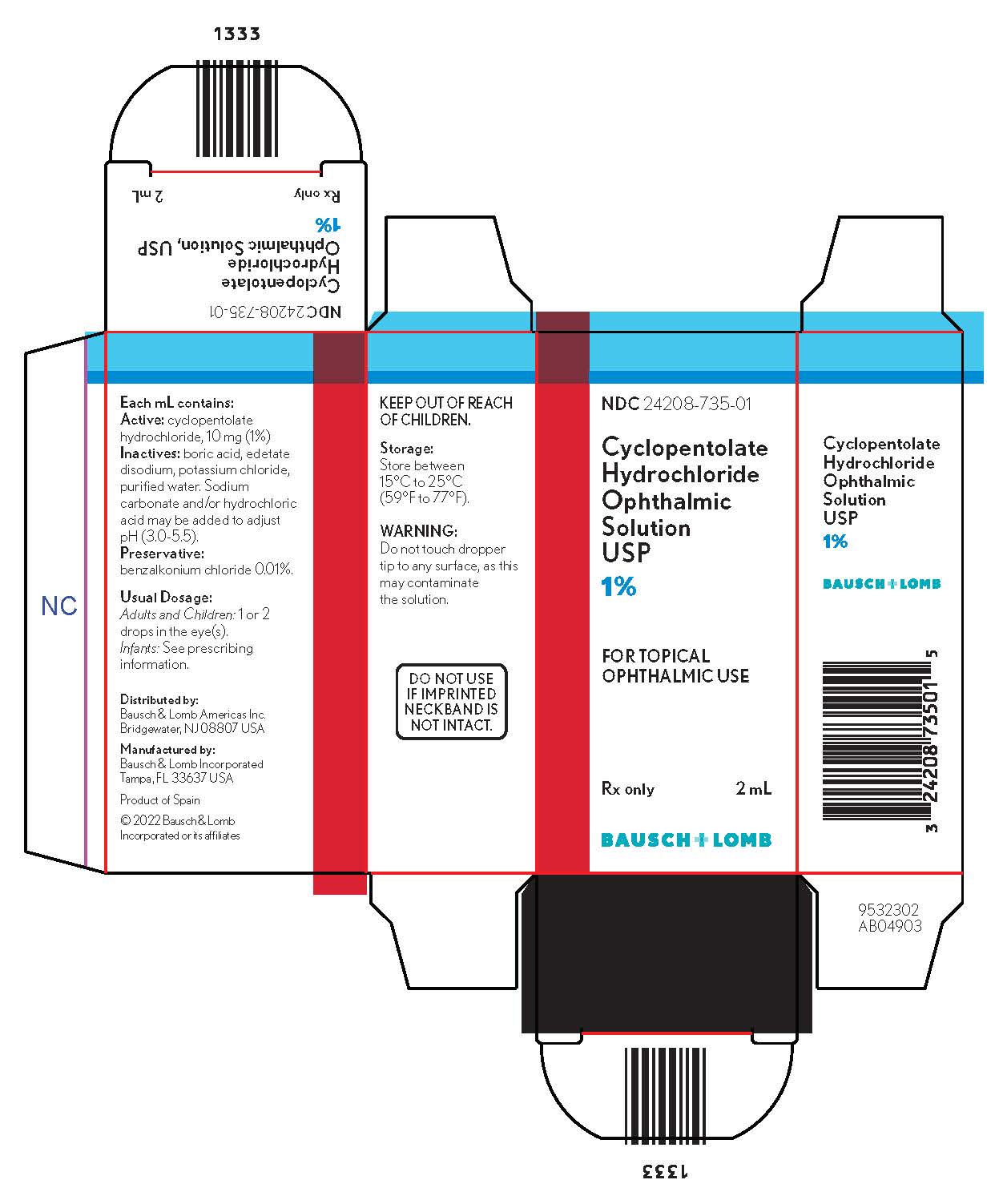 DRUG LABEL: Cyclopentolate Hydrochloride
NDC: 24208-735 | Form: SOLUTION/ DROPS
Manufacturer: Bausch & Lomb Incorporated
Category: prescription | Type: HUMAN PRESCRIPTION DRUG LABEL
Date: 20220929

ACTIVE INGREDIENTS: CYCLOPENTOLATE HYDROCHLORIDE 10 mg/1 mL
INACTIVE INGREDIENTS: BENZALKONIUM CHLORIDE; BORIC ACID; EDETATE DISODIUM; HYDROCHLORIC ACID; POTASSIUM CHLORIDE; WATER; SODIUM CARBONATE

Cyclopentolate
Hydrochloride
Ophthalmic
Solution
USP
1%
Rx only

DESCRIPTION

Cyclopentolate hydrochloride ophthalmic solution USP, 1% is an anticholinergic prepared as a sterile, borate buffered, solution for topical ocular use. The active ingredient is represented by the structural formula:

Molecular Weight = 327.85
Molecular Formula: C17H25NO3 • HCl

Established name: cyclopentolate hydrochloride
Chemical name: 2-(Dimethylamino) ethyl 1-hydroxy-α-phenylcyclopentaneacetate hydrochloride

Each mL contains:
Active: cyclopentolate hydrochloride, 10 mg (1%)

Inactives: boric acid, edetate disodium, potassium chloride, purified water. Sodium carbonate and/or hydrochloric acid (to adjust pH). The pH range is between 3.0 and 5.5.

Preservative: benzalkonium chloride 0.01%.

CLINICAL PHARMACOLOGY

This anticholinergic preparation blocks the responses of the sphincter muscle of the iris and the accommodative muscle of the ciliary body to cholinergic stimulation, producing pupillary dilation (mydriasis) and paralysis of accommodation (cycloplegia). It acts rapidly, but has a shorter duration than atropine. Maximal cycloplegia occurs within 25 to 75 minutes after instillation. Complete recovery of accommodation usually takes 6 to 24 hours. Complete recovery from mydriasis in some individuals may require several days. Heavily pigmented irides may require more doses than lightly pigmented irides.

INDICATIONS AND USAGE

Cyclopentolate hydrochloride ophthalmic solution is used to produce mydriasis and cycloplegia.

CONTRAINDICATIONS

Hypersensitive to any component of this preparation.

WARNINGS

FOR TOPICAL OPHTHALMIC USE. NOT FOR INJECTION. This preparation may cause Central Nervous System (CNS) disturbances. This is especially true in younger age groups, but may occur at any age, especially with the stronger cyclopentolate hydrochloride solutions. Infants are especially prone to CNS and cardiopulmonary side effects from cyclopentolate. To minimize absorption, use only 1 drop of a 1% cyclopentolate solution per eye, followed by pressure applied over the nasolacrimal sac for two to three minutes. Observe infants closely for at least 30 minutes following instillation.

Mydriatics may produce a transient elevation of intraocular pressure.

PRECAUTIONS

General:

The lacrimal sac should be compressed by digital pressure for two to three minutes after instillation to reduce excessive systemic absorption. Caution should be observed when considering use of this medication in the presence of Down’s syndrome.

Information for Patients:

Do not touch dropper tip to any surface, as this may contaminate the solution. A transient burning sensation may occur upon instillation. Patients should be advised not to drive or engage in other hazardous activities while pupils are dilated. Patients may experience sensitivity to light and should protect eyes in bright illumination during dilation. Parents should be warned not to get this preparation in their child’s mouth and to wash their own hands and the child’s hands following administration. Feeding intolerance may follow ophthalmic use of this product in infants. It is recommended that feeding be withheld for four (4) hours after examination.

Drug Interactions:

Cyclopentolate may interfere with the ocular anti-hypertensive action of carbachol, pilocarpine, or ophthalmic cholinesterase inhibitors.

Carcinogenesis, Mutagenesis, Impairment of Fertility:

Studies in animals or humans have not been conducted to evaluate the carcinogenic potential of cyclopentolate hydrochloride ophthalmic solution, USP.

Pregnancy:

Animal reproduction studies have not been conducted with cyclopentolate. It is also not known whether cyclopentolate can cause fetal harm when administered to a pregnant woman or can affect reproduction capacity. Cyclopentolate should be administered to a pregnant woman only if clearly needed.

Nursing Mothers:

It is not known whether this drug is excreted in human milk. Because many drugs are excreted in human milk, caution should be exercised when cyclopentolate hydrochloride is administered to a nursing woman.

Pediatric Use:

Use of cyclopentolate has been associated with psychotic reactions and behavioral disturbances in pediatric patients. Increased susceptibility to cyclopentolate has been reported in infants, young children, and in children with spastic paralysis or brain damage. These disturbances include ataxia, incoherent speech, restlessness, hallucinations, hyperactivity, seizures, disorientation as to time and place, and failure to recognize people. Feeding intolerance and necrotizing enterocolitis (in preterm infants) may follow ophthalmic use of this product in infants. It is recommended that feeding be withheld for four (4) hours after examination. Observe infants closely for at least 30 minutes (see WARNINGS).

Geriatric Use:

No overall differences in safety or effectiveness have been observed between elderly and younger patients.

ADVERSE REACTIONS

Ocular: Increased intraocular pressure, burning, photophobia, blurred vision, irritation, hyperemia, conjunctivitis, blepharoconjunctivitis, punctate keratitis, synechiae have been reported.

Non-ocular: Use of cyclopentolate has been associated with psychotic reactions and behavioral disturbances, usually in children, especially with 2% concentration. These disturbances include ataxia, incoherent speech, restlessness, hallucinations, hyperactivity, seizures, disorientation as to time and place, and failure to recognize people. This drug produces reactions similar to those of other anticholinergic drugs, but the CNS manifestations as noted above are more common. Other toxic manifestations of anticholinergic drugs are skin rash, abdominal distention in infants, necrotizing enterocolitis (in preterm infants), unusual drowsiness, tachycardia, hyperpyrexia, vasodilation, urinary retention, diminished gastrointestinal motility and decreased secretion in salivary and sweat glands, pharynx, bronchi and nasal passages. Severe manifestations of toxicity include coma, medullary paralysis and death.

To report SUSPECTED ADVERSE REACTIONS, contact Bausch & Lomb Incorporated at 1-800-553-5340 or FDA at 1-800-FDA-1088 or www.fda.gov/medwatch.

OVERDOSAGE

Excessive dosage may produce behavioral disturbances, tachycardia, hyperpyrexia, hypertension, elevated intraocular pressure, vasodilation, urinary retention, diminished gastrointestinal motility and decreased secretion in salivary and sweat glands, pharynx, bronchi and nasal passages. Patients exhibiting signs of overdosage should receive supportive care and monitoring.

DOSAGE AND ADMINISTRATION

Adults: Instill one or two drops of 1% solution in the eye which may be repeated in five to ten minutes if necessary. Complete recovery usually occurs in 24 hours. Complete recovery from mydriasis in some individuals may require several days.

Children: Instill one or two drops of 1% solution in the eye, which may be repeated five to ten minutes later by a second application of 1% solution if necessary.

Individuals with heavily pigmented irides may require higher strengths.

HOW SUPPLIED

Cyclopentolate hydrochloride ophthalmic solution USP, 1% is available in multidose plastic squeeze bottles with a controlled drop tip and red cap in the following sizes:

2 mL bottle - NDC 24208-735-01
15 mL bottle - NDC 24208-735-06

Storage:

Store between 15°C to 25°C (59°F to 77°F).

KEEP OUT OF REACH OF CHILDREN.

Distributed by:
Bausch & Lomb Americas Inc.
Bridgewater, NJ 08807 USA
Manufactured by:
Bausch & Lomb Incorporated
Tampa, FL 33637 USA
© 2022 Bausch & Lomb Incorporated or its affiliates
Rev. 09/2022

9114607 (Folded)
9114707 (Flat)

PACKAGE/LABEL PRINCIPAL DISPLAY PANEL

NDC 24208-735-01

Cyclopentolate
Hydrochloride
Ophthalmic
Solution
USP
1%
FOR TOPICAL
OPHTHALMIC USE

Rx only

2 mL

BAUSCH + LOMB

9532302
AB04903